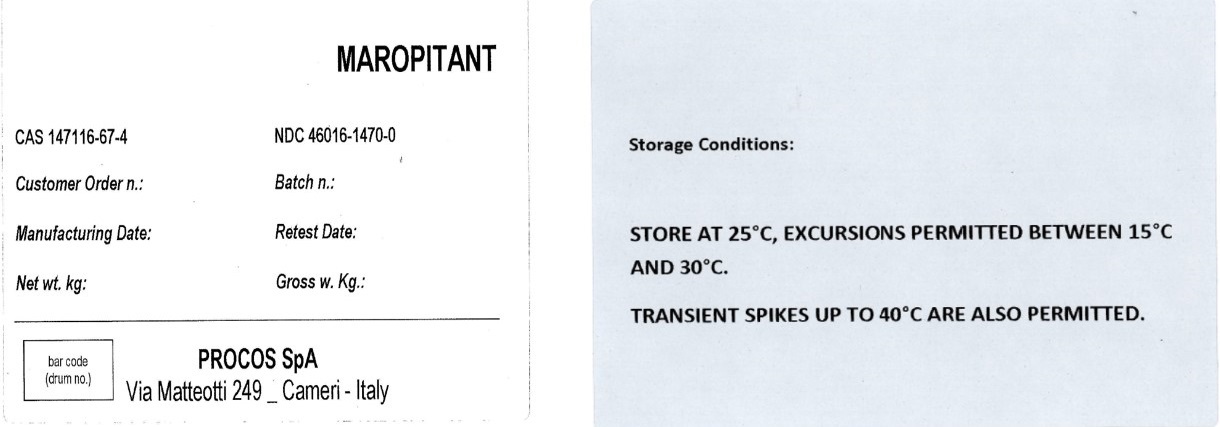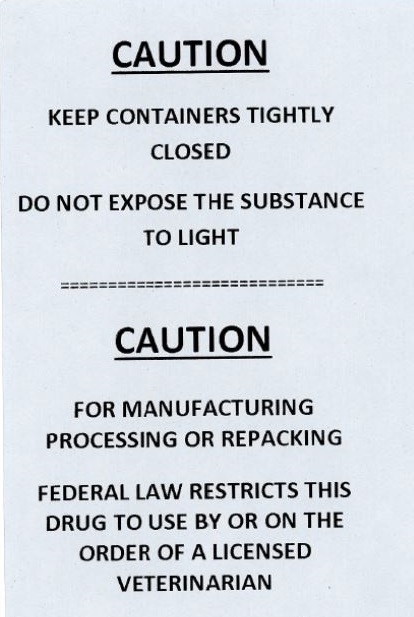 DRUG LABEL: Maropitant
NDC: 46016-1470 | Form: POWDER
Manufacturer: PROCOS SpA
Category: other | Type: BULK INGREDIENT - ANIMAL DRUG
Date: 20220322

ACTIVE INGREDIENTS: MAROPITANT 50 kg/50 kg

MAROPITANT

PACKAGE LABEL

MAROPITANT

CAS 147116-67-4

NDC 46016-1470-0

PROCOS SpA

Via Matteotti 249 Cameri - Italy

CAUTION

KEEP CONTAINERS TIGHTLY CLOSED

DO NOT EXPOSE THE SUBSTANCE TO LIGHT

CAUTION

FOR MANUFACTURING, PROCESSING OR REPACKING

FEDERAL LAW RESTRICTS THIS DRUG TO USE BY OR ON THE ORDER OF A LICENSED VETERINARIAN

Storage Conditions:

STORE AT 25°C, EXCURSIONS PERMITTED BETWEEN 15°C AND 30°C.

TRANSIENT SPIKES UP TO 40°C ARE ALSO PERMITTED.